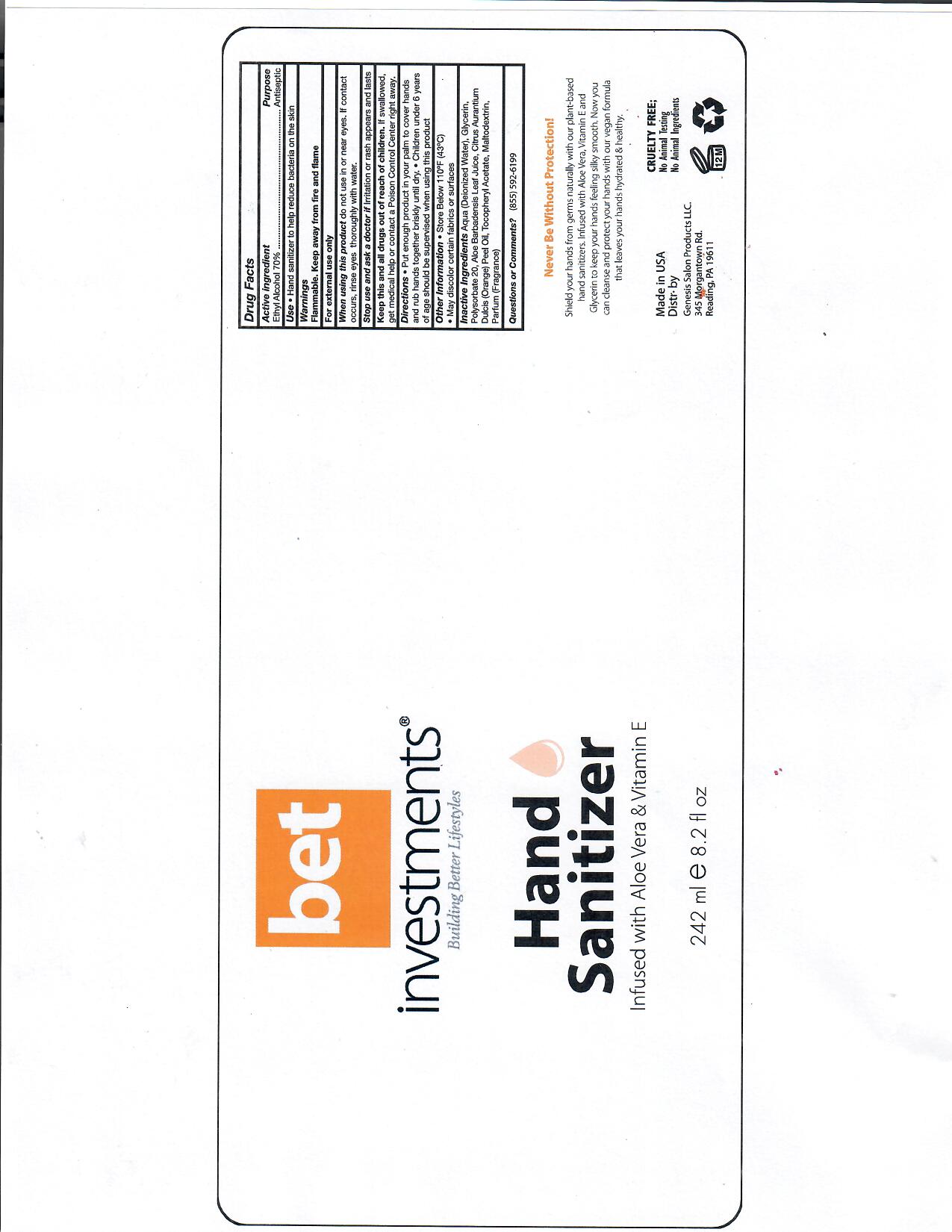 DRUG LABEL: Hand SanitizerBET
NDC: 76650-120 | Form: SOLUTION
Manufacturer: Genesis Salon Products LLC
Category: otc | Type: HUMAN OTC DRUG LABEL
Date: 20200709

ACTIVE INGREDIENTS: ALCOHOL 70 mL/100 mL
INACTIVE INGREDIENTS: GLYCERIN; ALOE; WATER; POLYSORBATE 20; ORANGE PEEL; maltodextrin

This is a hand sanitizer manufactured according to the Temporary Policy for Preparation of Certain Alcohol-Based Hand Sanitizer Products During the Public Health Emergency (CoViD-19); Guidance for Industry.

The hand sanitizer is manufactured using only the following United States Pharmacopoeia (USP) grade ingredients in the preparation of the product (percentage in final product formulation) consistent with World Health Organization (WHO) recommendations:

1. Alcohol (ethanol) (USP or Food Chemical Codex (FCC) grade) (70%) in an aqueous solution denatured according to Alcohol and Tobacco Tax and Trade Bureau regulations in 27 CFR part 20.
2. Glycerin
3. Sterile distilled water.

Active Ingredient(s)

Alcohol 70%. Purpose: Antiseptic

Purpose

Antiseptic, Hand Sanitizer

Use

Hand Sanitizer to help reduce bacteria on the skin.

Warnings

For external use only. Flammable. Keep away from heat or flame

Do not use

- in or near eyes.

When using this product do not use in or near eyes. If contact occurs, rinse eyes thoroughly with water.
Stop use and ask a doctor if irritation or rash appears and lasts.
Keep this and all drugs out of reach of children. If swallowed, get medical help or contact a Poison Control Center right away.

Stop use and ask a doctor if irritation or rash appears and lasts.

Keep out of reach of children. If swallowed, get medical help or contact a Poison Control Center right away.

Directions

- Put enough product in your palm to cover hands and rub together briskly until dry.
- Children under 6 years of age should be supervised when using this product.

Other information

- Store below 110F (43C)

Inactive ingredients

deionized water, glycerin, polysorbate 20, aloe barbadensis leaf juice, citrus aurantium dulcis peel oil, tocopheryl acetate, maltodextrin, fragrance